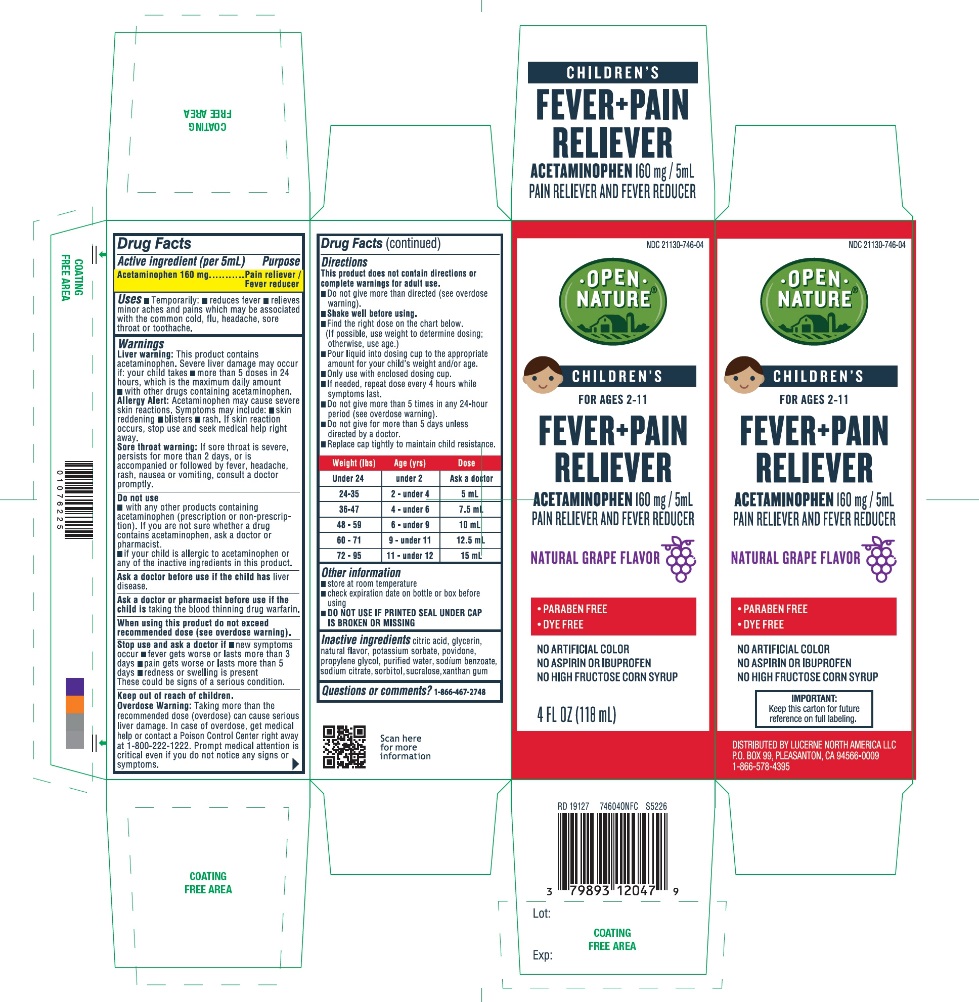 DRUG LABEL: better living brands childrens fever and pain reliver
NDC: 21130-746 | Form: SUSPENSION
Manufacturer: BETTER LIVING BRANDS LLC
Category: otc | Type: HUMAN OTC DRUG LABEL
Date: 20251120

ACTIVE INGREDIENTS: ACETAMINOPHEN 160 mg/5 mL
INACTIVE INGREDIENTS: ANHYDROUS CITRIC ACID; GLYCERIN; POTASSIUM SORBATE; POVIDONE, UNSPECIFIED; PROPYLENE GLYCOL; WATER; SODIUM BENZOATE; SODIUM CITRATE, UNSPECIFIED FORM; SORBITOL; SUCRALOSE; XANTHAN GUM

Better Living Brands Children’s Fever + Pain Reliever

Active ingredient (per 5 mL)

Acetaminophen 160 mg

Purpose

Pain reliever/Fever reducer

Uses

Temporarily:

- reduces fever
- relieves minor aches and pains which may be associated with the common cold, flu, headache, sore throat or toothache.

Warnings

Liver warning:This product contains acetaminophen. Severe liver damage may occur if your child takes

- more than 5 doses in 24 hours, which is the maximum daily amount
- with other drugs containing acetaminophen

Allergy alert:Acetaminophen may cause severe skin reactions. Symptoms may include:

- skin reddening
- blisters
- rash

If a skin reaction occurs, stop use and seek medical help right away.

Sore throat warning:If sore throat is severe, persists for more than 2 days, or is accompanied or followed by fever, headache, rash, nausea, or vomiting, consult a doctor promptly.

Do not use

- with any other drug containing acetaminophen (prescription or nonprescription). If you are not sure whether a drug contains acetaminophen, ask a doctor or pharmacist.
- if your child is allergic to acetaminophen or any of the inactive ingredients in this product.

Ask a doctor before use if your child has

liver disease

Ask a doctor or pharmacist before use if the child is

taking the blood thinning drug warfarin

When using this product

do not exceed recommended dose (see overdose warning)

Stop use and ask a doctor if

- new symptoms occur
- pain gets worse or lasts more than 3 days
- fever gets worse or lasts more than 5 days
- redness or swelling is present

These could be signs of a serious condition.

Keep out of reach of children.

Overdose warning:Taking more than the recommended dose(overdose) can cause serious liver damage. In case of overdose, get medical help or contact a Poison Control Center right away (1-800-222-1222). Prompt medical attention is critical even if you do not notice any signs or symptoms.

Directions

- This product does not contain directions or complete warnings for adult use
- Do not give more than directed (see overdose warning).
- Shake well before using
- Find right dose on chart below. (If possible, use weight to determine dosing; otherwise, use age.)
- Pour liquid into dosing cup to the appropriate amount for your child’s weight and/or age.
- Only use with enclosed dosing cup.
- If needed, repeat dose every 4 hours while symptoms last.
- Do not give more than 5 times in any 24-hour period (see overdose warning).
- Do not give more than 5 days unless directed by a doctor.
- Replace cap tightly to maintain child resistance.

Weight (lbs) | Age (yrs) | Dose
under 24 | under 2 | Ask a doctor
24-35 | 2- under 4 | 5 mL
36-47 | 4- under 6 | 7.5 mL
48-59 | 6- under 9 | 10 mL
60-71 | 9- under 11 | 12.5 mL
72-95 | 11- under 12 | 15 mL

Other information

- Store at room temperature
- Check expiration date on bottle or box before using
- DO NOT USE IF PRINTED NECKBAND IS BROKEN OR MISSING

Inactive ingredients

citric acid, glycerin, natural flavor, potassium sorbate, povidone, propylene glycol, purified water, sodium benzoate, sodium citrate, sorbitol, sucralose, xanthan gum

Questions or comments?

1-866-467-2748

Principal Display Panel

NDC 21130-746-04

Compare to the active ingredient in Little Remedies®Children’s Fever + Pain Reliever*

Children’s Fever + Pain Reliever

ACETAMINOPHEN160 mg/ 5mL

PAIN RELIEVER AND FEVER REDUCER

- PARABEN FREE
- DYE FREE
- NO ARTIFICIAL COLOR
- NO ASPIRIN OR LBUPROFEN
- NO HIGH FRUCTOSE CORN SYRUP

For Age 2-11

NATURAL GRAPE FLAVOR

4 FL. OZ. (118 mL)

DISTRIBUTED BY:

LUCERNE NORTH AMERICA LLC

P.O. BOX 99, PLEASANTON, CA 94566-0009

1-866-578-4935

Keep this carton for future reference on full labeling.

*This product is not manufactured or distributed by Prestige Consumer trademark Little Remedies®Children’s Fever + Pain Reliever.